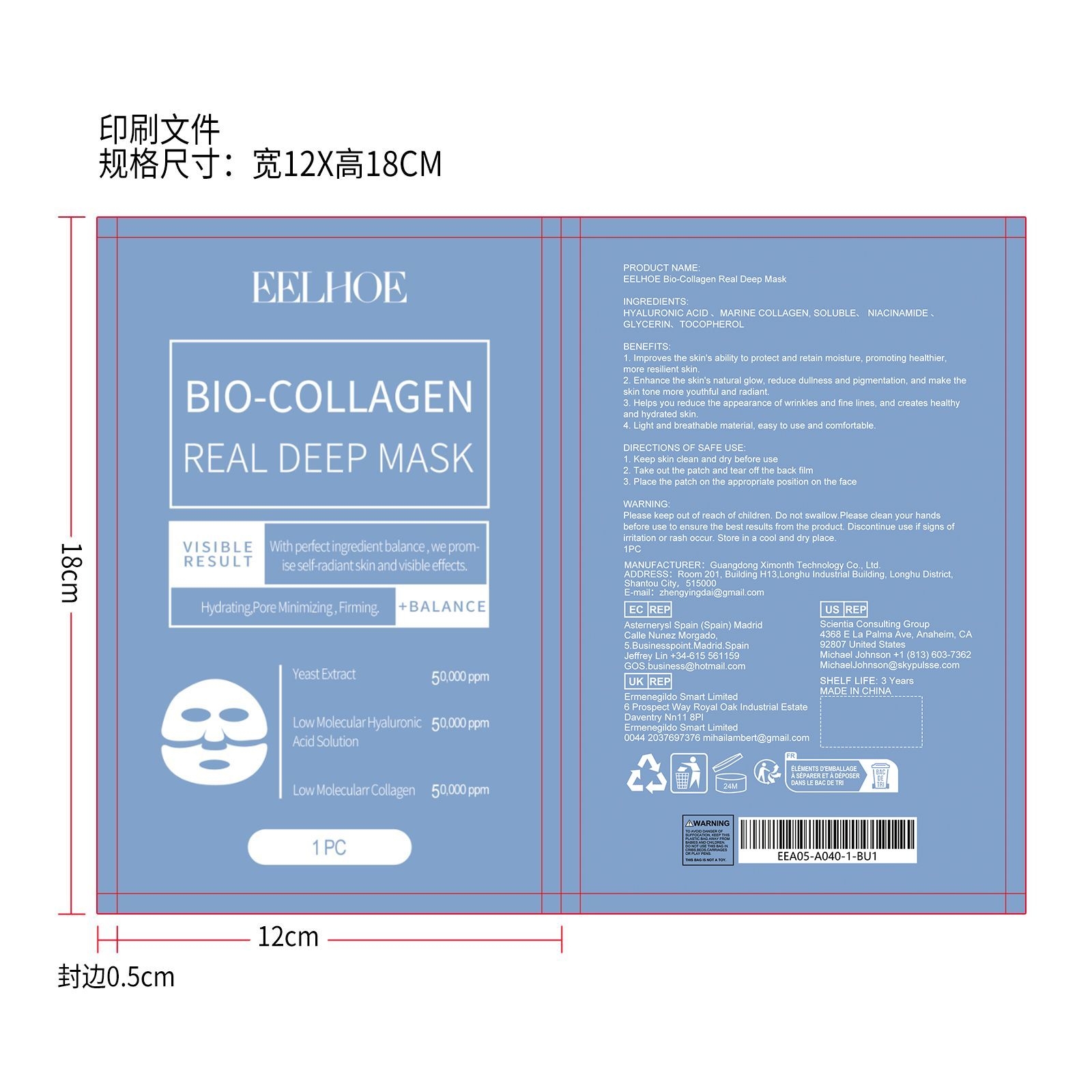 DRUG LABEL: EELHOE Bio-Collagen Real Deep Mask
NDC: 84660-041 | Form: PATCH
Manufacturer: Guangdong Ximonth Technology Co., Ltd.
Category: otc | Type: HUMAN OTC DRUG LABEL
Date: 20241009

ACTIVE INGREDIENTS: HYALURONIC ACID 14.5 g/58 g; NIACINAMIDE 11.6 g/58 g; TOCOPHEROL 8.7 g/58 g; MARINE COLLAGEN, SOLUBLE 5.8 g/58 g
INACTIVE INGREDIENTS: GLYCERIN 17.4 g/58 g

Active Ingredient(s)

HYALURONIC ACID 、MARINE COLLAGEN, SOLUBLE、 NIACINAMIDE 、TOCOPHEROL

Purpose

1. Improves the skin's ability to protect and retain moisture, promoting healthier, more resilient skin.
2. Enhance the skin's natural glow, reduce dullness and pigmentation, and make the skin tone more youthful and radiant.
3. Helps you reduce the appearance of wrinkles and fine lines, and creates healthy and hydrated skin.
4. Light and breathable material, easy to use and comfortable.

Use

1. Keep skin clean and dry before use
2. Take out the patch and tear off the back film
3. Place the patch on the appropriate position on the face

STOP USE

Discontinue use if signs of irritation or rash occur.

Do not use

Discontinue use if signs of irritation or rash occur.

Warnings

Please keep out of reach of children.Do not swallow.Please clean your hands before use to ensure the best results from the product.Discontinue use if signs of irritation or rash occur.Store in a cool and dry place.

KEEP OUT OF REACH OF CHILDREN

Please keep out of reach of children. Do not swallow.

STORAGE AND HANDLING

Avoid freezing and excessive heat above 40C (104F) ）
Store in a cool and dry place.

INACTIVE INGREDIENT

GLYCERIN